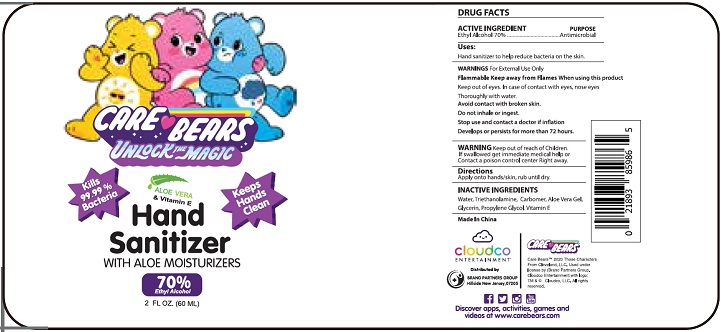 DRUG LABEL: Care Bears
NDC: 77706-002 | Form: GEL
Manufacturer: BRAND PARTNERS GROUP
Category: otc | Type: HUMAN OTC DRUG LABEL
Date: 20200514

ACTIVE INGREDIENTS: ALCOHOL 70 mL/100 mL
INACTIVE INGREDIENTS: WATER; TROLAMINE; CARBOMER HOMOPOLYMER, UNSPECIFIED TYPE; ALOE VERA LEAF; GLYCERIN; PROPYLENE GLYCOL; ALPHA-TOCOPHEROL ACETATE

Active Ingredient

Ethyl Alcohol 70%

Purpose

Antimicrobial

Uses

Hand sanitizer to help reduce bacteria on the skin.

Warnings

Flammable Keep away from Flames.

When using this product Keep out of eyes. In case of contact with eyes, nose eyes Thoroughly with water.

Avoid contact with broken skin.

Do not inhale or ingest.

Stop use and contact a doctor if irritation develops or persists for more than 72 hours.

Keep out of reach of Children. If swallowed get immediate medical help or contact a poison control center right away.

Directions

Apply onto hands/skin, rub until dry.

Inactive ingredients

Water, Triethanolamine, Carbomer, Aloe Vera Gel, Glycerin, Propylene Glycol. Vitamin E

Package Label - Principal Display Panel

Label 60 mL